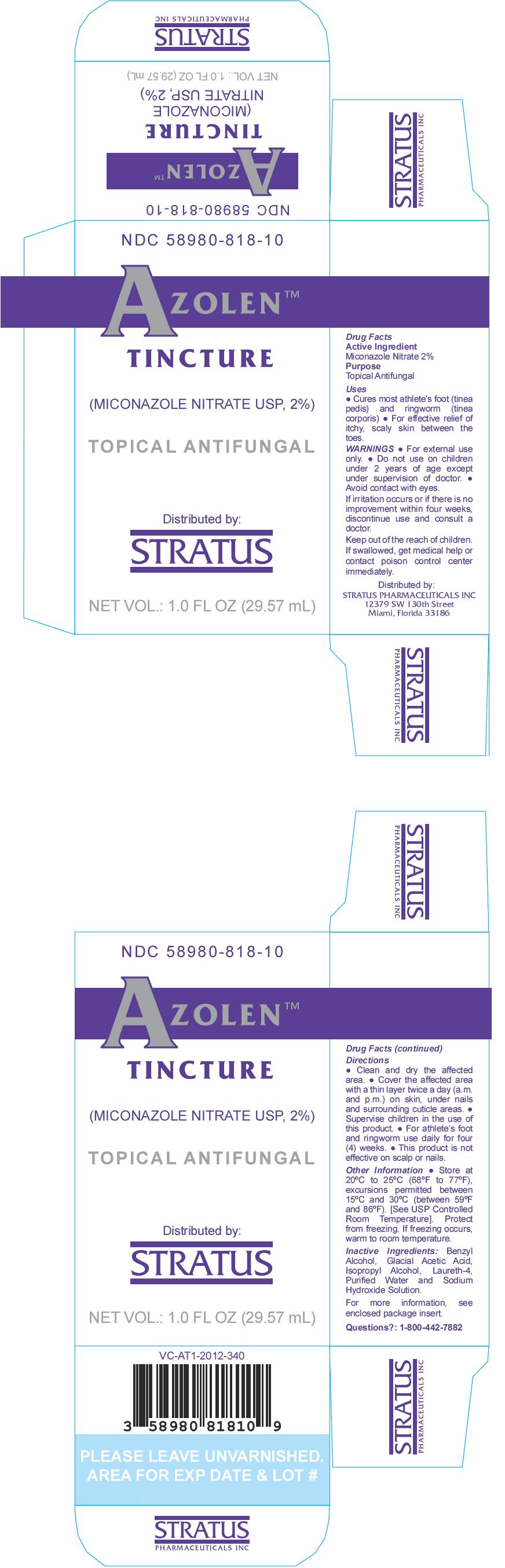 DRUG LABEL: Azolen
NDC: 58980-818 | Form: TINCTURE
Manufacturer: Stratus Pharmaceuticals, Inc.
Category: otc | Type: HUMAN OTC DRUG LABEL
Date: 20251030

ACTIVE INGREDIENTS: Miconazole Nitrate 20 mg/1 mL
INACTIVE INGREDIENTS: Water; Benzyl Alcohol; Acetic Acid; Isopropyl Alcohol; Laureth-4; Sodium Hydroxide

AZOLEN™
TINCTURE

Drug Facts

Active Ingredient

Miconazole Nitrate 2%

Purpose

Topical Antifungal

Uses

- Cures most athlete's foot (tinea pedis) and ringworm (tinea corporis)
- For effective relief of itchy, scaly skin between the toes.

WARNINGS

- For external use only.

- Do not use on children under 2 years of age except under supervision of doctor.

WHEN USING

- Avoid contact with eyes.

STOP USE

If irritation occurs or if there is no improvement within four weeks, discontinue use and consult a doctor.

KEEP OUT OF REACH OF CHILDREN

Keep out of the reach of children. If swallowed, get medical help or contact poison control center immediately.

Directions

- Clean and dry the affected area.
- Cover the affected area with a thin layer twice a day (a.m. and p.m.) on skin, under nails and surrounding cuticle areas.
- Supervise children in the use of this product.
- For athlete's foot and ringworm use daily for four (4) weeks.
- This product is not effective on scalp or nails.

Other Information

- Store at 25°C (77°F); excursions permitted to 15°C - 30°C (59° - 86°F). [See USP Controlled Room Temperature]. Protect from freezing. If freezing occurs, warm to room temperature.

Inactive Ingredients

Benzyl Alcohol, Glacial Acetic Acid, Isopropyl Alcohol, Laureth-4, Purified Water and Sodium Hydroxide Solution.

For more information, see enclosed package insert.

Questions?

1-800-442-7882

Distributed by:
STRATUS PHARMACEUTICALS INC
12379 SW 130th Street
Miami, Florida 33186

PRINCIPAL DISPLAY PANEL - 29.57 mL Bottle Carton

NDC 58980-818-10

AZOLEN™
TINCTURE

(MICONAZOLE NITRATE USP, 2%)

TOPICAL ANTIFUNGAL

Distributed by:
STRATUS

NET VOL.: 1.0 FL OZ (29.57 mL)